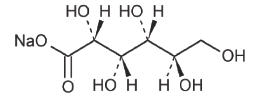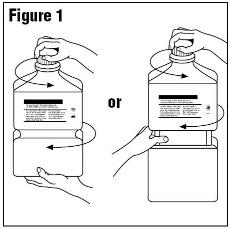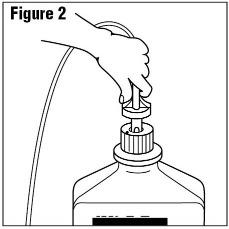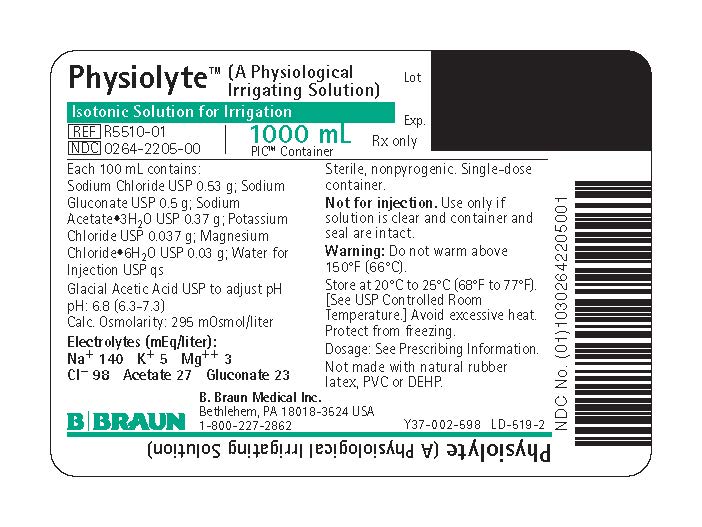 DRUG LABEL: Physiolyte
NDC: 0264-2205 | Form: IRRIGANT
Manufacturer: B. Braun Medical Inc.
Category: prescription | Type: HUMAN PRESCRIPTION DRUG LABEL
Date: 20230926

ACTIVE INGREDIENTS: SODIUM CHLORIDE 0.53 g/100 mL; SODIUM GLUCONATE 0.5 g/100 mL; SODIUM ACETATE 0.37 g/100 mL; POTASSIUM CHLORIDE 0.037 g/100 mL; MAGNESIUM CHLORIDE 0.03 g/100 mL
INACTIVE INGREDIENTS: WATER; ACETIC ACID

Y36-002-961 LD-515-2
Package Insert
PIC™ (Plastic Irrigation Containers)
Physiolyte™
(A Physiological Irrigating Solution)

Balanced Electrolyte Solution for Irrigation.
For All General Irrigation, Washing, and Rinsing Purposes.
Not for Injection by Usual Parenteral Route.

Rx only

DESCRIPTION

Physiolyte is a sterile, nonpyrogenic solution of electrolytes in water for injection intended only for sterile irrigation, washing, and rinsing purposes.

Each 100 mL contains:
Sodium Chloride USP 0.53 g; Sodium Gluconate USP 0.5 g
Sodium Acetate Trihydrate USP 0.37 g; Potassium Chloride
USP 0.037 g; Magnesium Chloride Hexahydrate USP 0.03 g
Water for Injection USP qs
Glacial Acetic Acid USP has been added to adjust the pH

pH: 6.8 (6.3–7.3)
Calculated Osmolarity: The solution is isotonic (295 mOsmol/liter)

Concentration of Electrolytes (mEq/liter): Sodium 140
Potassium 5; Magnesium 3; Chloride 98; Acetate (CH3COO^−) 27
Gluconate (HOCH2(CHOH)4COO^−) 23

It contains no bacteriostat, antimicrobial agent or added buffer (except for pH adjustment) and is intended only for use as a single-dose or short procedure irrigation. When smaller volumes are required the unused portion should be discarded.

Physiolyte may be classified as a sterile irrigant, wash, rinse and pharmaceutical vehicle.

The formulas of the active ingredients are:

Ingredients | Molecular Formula | Molecular Weight
Sodium Chloride USP | NaCl | 58.44
Sodium Acetate Trihydrate USP | CH3COONa•3H2O | 136.08
Potassium Chloride USP | KCl | 74.55
Magnesium Chloride Hexahydrate USP | MgCl2•6H2O | 203.30
Sodium Gluconate USP |  | 218.14

The plastic container is a copolymer of ethylene and propylene formulated and developed for parenteral drugs. The copolymer contains no plasticizers and exhibits virtually no leachability. The plastic container is also virtually impermeable to vapor transmission and therefore, requires no overwrap to maintain the proper drug concentration. The safety of the plastic container has been confirmed by biological evaluation procedures. The material passes Class VI testing as specified in the U.S. Pharmacopeia for Biological Tests. The safety of the plastic has been confirmed by tests in animals according to USP biological standards for plastic containers.

Not made with natural rubber latex, PVC or DEHP.

CLINICAL PHARMACOLOGY

Physiolyte exerts a mechanical cleansing action for sterile irrigation of body cavities, tissues or wounds, indwelling urethral catheters and surgical drainage tubes, and for washing, rinsing or soaking surgical dressings, instruments and laboratory specimens. It also serves as a vehicle for drugs used for irrigation or other pharmaceutical preparations.

Physiolyte provides an isotonic calcium-free balanced electrolyte irrigation with the same ionic composition as Isolyte® S (Multi-Electrolyte Solution) a multiple electrolyte solution for IV replacement of acute extracellular fluid losses.

Physiological irrigation solutions are considered generally compatible with living tissues and organs.

Sodium, the major cation of the extracellular fluid, functions primarily in the control of water distribution, fluid balance, and osmotic pressure of body fluids. Sodium is also associated with chloride and bicarbonate in the regulation of the acid-base equilibrium of body fluid.

Potassium, the principal cation of intracellular fluid, participates in carbohydrate utilization and protein synthesis, and is critical in the regulation of nerve conduction and muscle contraction, particularly in the heart.

Chloride, the major extracellular anion, closely follows the metabolism of sodium, and changes in the acid-base balance of the body are reflected by changes in the chloride concentration.

Magnesium, a principal cation of soft tissue, is primarily involved in enzyme activity associated with the metabolism of carbohydrates and protein. Magnesium is also involved in neuromuscular and cardiac conduction and irritability.

Gluconate and acetate are organic ions which are hydrogen ion acceptors and contribute bicarbonate during their metabolism to carbon dioxide and water, and serve as alkalinizing agents.

Water is an essential constituent of all body tissues and accounts for approximately 70% of total body weight. Average normal adult daily requirement ranges from two to three liters (1.0 to 1.5 liters each for insensible water loss by perspiration and urine production).

Water balance is maintained by various regulatory mechanisms. Water distribution depends primarily on the concentration of electrolytes in the body compartments and sodium (Na^+) plays a major role in maintaining physiologic equilibrium.

INDICATIONS AND USAGE

Physiolyte™ (A Physiological Irrigating Solution) is indicated for all general irrigation, washing, and rinsing purposes which permit use of a sterile, nonpyrogenic electrolyte solution.

CONTRAINDICATIONS

Physiolyte is not for injection by usual parenteral routes.

An electrolyte solution should not be used for irrigation during electrosurgical procedures.

WARNINGS

FOR IRRIGATION ONLY. NOT FOR INJECTION.

Irrigating fluids have been demonstrated to enter the systemic circulation in relatively large volumes; thus, irrigation solutions must be regarded as systemic drugs. Absorption of large amounts can cause fluid and/or solute overload resulting in dilution of serum electrolyte concentrations, overhydration, congested states or pulmonary edema.

The risk of dilutional states is inversely proportional to the electrolyte concentrations of the administered parenteral solutions. The risk of solute overload causing congested states with peripheral and pulmonary edema is directly proportional to the electrolyte concentrations.

Do not warm above 150°F (66°C).

After opening container, it's contents should be used promptly to minimize the possibility of bacterial growth or pyrogen formation.

Discard unused portion of irrigating solution since it contains no preservatives.

PRECAUTIONS

General

Use aseptic technique when preparing and administering sterile irrigation solutions for irrigating body cavities, wounds and urethral catheters or for wetting dressings that come in contact with the body tissues. Use only if solution is clear and container and seal are intact.

Do not use for irrigation that may result in absorption of large amounts into the blood.

Caution should be observed when the solution is used for continuous irrigation or allowed to "dwell" inside body cavities because of possible absorption into the blood stream and the production of circulatory overload.

When used as a "pour" irrigation, no part of the contents should be allowed to contact the surface below the outer protected thread area of the plastic irrigation container. When used for irrigation via appropriate irrigation equipment, the administration set should be attached promptly. Unused portions should be discarded and a fresh container of appropriate size used for the start up of each cycle or repeat procedure. For repeated irrigations of urethral catheters, a separate container should be used for each patient.

Carcinogenesis, Mutagenesis, Impairment of Fertility

Studies with Physiolyte™ (A Physiological Irrigating Solution) have not been performed to evaluate carcinogenic potential, mutagenic potential, or effects on fertility.

Pregnancy

Teratogenic Effects

Animal reproduction studies have not been conducted with Physiolyte (A Physiological Irrigating Solution). It is also not known whether Physiolyte (A Physiological Irrigating Solution) can cause fetal harm when administered to a pregnant woman or can affect reproduction capacity. Physiolyte (A Physiological Irrigating Solution) should be given to a pregnant woman only if clearly needed.

Nursing Mothers

Caution should be exercised when Physiolyte is administered to a nursing woman.

Pediatric Use

The safety and effectiveness of Physiolyte in pediatric patients have not been established. Its limited use in pediatric patients has been inadequate to fully define proper dosage and limitations for use.

Geriatric Use

Clinical studies of Physiolyte (A Physiological Irrigating Solution) have not been performed to determine whether patients over 65 years of age respond differently from younger subjects. Other reported clinical experience has not identified differences in responses between elderly and younger patients. In general, dose selection for an elderly patient should be cautious, reflecting the greater frequency of decreased hepatic, renal, or cardiac function, and of concomitant disease or other drug therapy.

This drug is known to be substantially excreted by the kidney, and the risk of toxic reactions to this drug may be greater in patients with impaired renal function. Because elderly patients are more likely to have decreased renal function, care should be taken in dose selection, and it may be useful to monitor renal function.

Use in Patients with Renal Insufficiency/Failure

Clinical studies of Physiolyte (A Physiological Irrigation Solution) have not been performed to determine whether patients with renal failure respond differently from those with normal renal function. Given the potential for systemic absorption, the risk of toxic reactions to this drug may be greater in patients with impaired renal function. Increased caution should be exercised when administering Physiolyte to patients with impaired fluid and electrolyte homeostasis.

ADVERSE REACTIONS

Possible adverse effects arising from the irrigation of body cavities, tissues, or indwelling catheters and tubes can be minimized when proper procedures are followed. Displaced catheters or drainage tubes can lead to irrigation or infiltration of unintended structures or cavities. Excessive volume or pressure during irrigation of closed cavities may cause undue distension or disruption of tissues. Accidental contamination from careless technique may transmit infection.

If an adverse reaction does occur, discontinue administration of the irrigant, evaluate the patient, institute appropriate therapeutic countermeasures, and save the remainder of the fluid for examination if deemed necessary.

OVERDOSAGE

In the event of overhydration or solute overload, reevaluate the patient's condition, and institute appropriate corrective treatment. Intravascular volume overload may respond to hemodialysis. See WARNINGS, PRECAUTIONS, and ADVERSE REACTIONS.

DOSAGE AND ADMINISTRATION

As required for irrigation.

The dose is dependent upon the capacity or surface area of the structure to be irrigated and the nature of the procedure. When used as a vehicle for other drugs, the directions of the additive's manufacturer should be followed.

Some additives may be incompatible. Consult with pharmacist. When introducing additives, use aseptic techniques. Mix thoroughly. Do not store.

Solutions should be inspected visually for particulate matter and discoloration prior to administration, whenever solution and container permits.

HOW SUPPLIED

Physiolyte™ (A Physiological Irrigating Solution) is supplied sterile and nonpyrogenic in 1000 mL PIC™ (Plastic Irrigation Containers) packaged 16 per case.

NDC | REF | Size
Physiolyte (A Physiological Irrigating Solution)
0264-2205-00 | R5510-01 | 1000 mL

STORAGE AND HANDLING

Exposure of pharmaceutical products to heat should be minimized. Avoid excessive heat. Protect from freezing. Store at 20°C to 25°C (68°F to 77°F); excursions permitted between 15°C to 30°C (59°F to 86°F). [See USP Controlled Room Temperature.] However, brief exposure up to 40°C does not adversely affect the product.

Do not warm above 150°F (66°C).

Revised: June 2023
Isolyte is a registered trademark and Physiolyte and PIC are trademarks of
B. Braun Medical Inc.

Directions for Use of PIC™ (Plastic Irrigation Container)

Not for injection.

Aseptic technique is required.

1. Caution – Before use, perform the following checks:

(a) Read the label. Ensure solution is the one ordered and is within the expiration date.
(b) Invert container and inspect the solution in good light for cloudiness, haze, or particulate
matter; check the container for leakage or damage. Any container which is suspect should
not be used.

Use only if solution is clear and container and seal are intact.

Single-dose container. Discard unused portion.

2. Outer Closure Removal – Grasp the container with one hand and turn the breakaway
ring counterclockwise with the other hand until slight resistance is felt. Then, twisting the
container in the opposite direction, turn the breakaway ring sharply until the entire outer
cap is loose and can be lifted off. (Figure 1)

3. Connect the administration set through the sterile set port according to set instructions (Figure 2) or remove
screw cap and pour.

4. Do not warm above 150°F (66°C) to assure minimal bottle distortion. Keep bottles upright.

B. Braun Medical Inc.
Bethlehem, PA 18018-3524 USA
1-800-227-2862

PRINCIPAL DISPLAY PANEL - 1000 mL Container Label

Physiolyte™ (A Physiological Irrigating Solution)
Isotonic Solution for Irrigation

REF R5510-01
NDC 0264-2205-00

1000 mL
PIC™ Container

Rx only

Lot
Exp.

Each 100 mL contains:
Sodium Chloride USP 0.53 g;
Sodium Gluconate USP 0.5 g;
Sodium Acetate•3H2O USP 0.37 g;
Potassium Chloride USP 0.037 g;
Magnesium Chloride•6H2O USP 0.03 g;
Water for Injection USP qs
Glacial Acetic Acid USP to adjust pH
pH: 6.8 (6.3-7.3)
Calc. Osmolarity: 295 mOsmol/liter
Electrolytes (mEq/liter):
Na^+ 140 K^+ 5 Mg^+^+ 3
CI^− 98 Acetate 27 Gluconate 23

Sterile, nonpyrogenic. Single-dose container.

Not for injection. Use only if solution is clear and container and seal are intact.

Warning: Do not warm above 150°F (66°C).

Store at 20°C to 25°C (68°F to 77°F). [See USP Controlled Room Temperature.] Avoid excessive heat. Protect from freezing.

Dosage: See Prescribing Information.

Not made with natural rubber latex, PVC or DEHP.

B. Braun Medical Inc.
Bethlehem, PA 18018-3524 USA
1-800-227-2862

Y37-002-598 LD-519-2

Physiolyte (A Physiological Irrigating Solution)